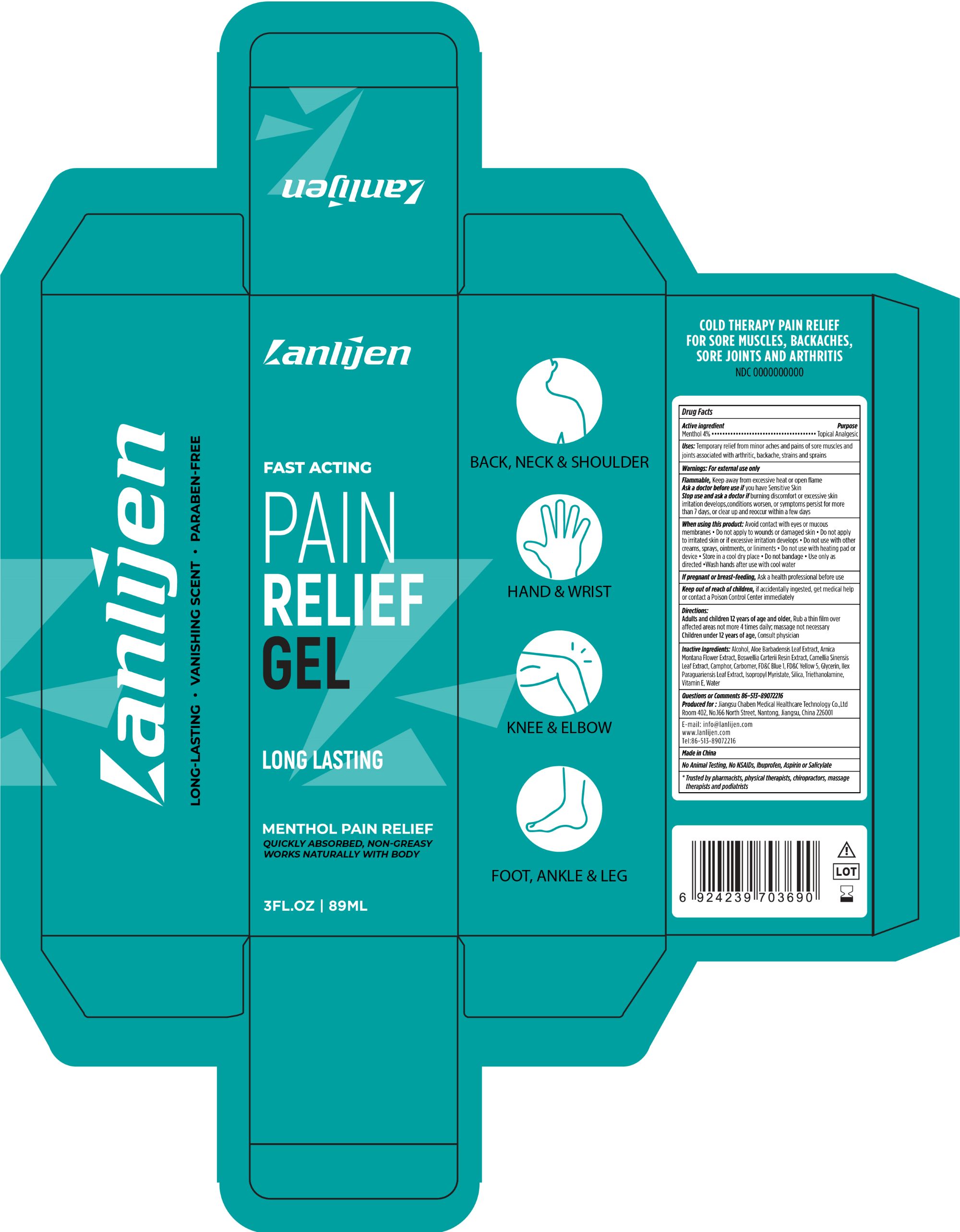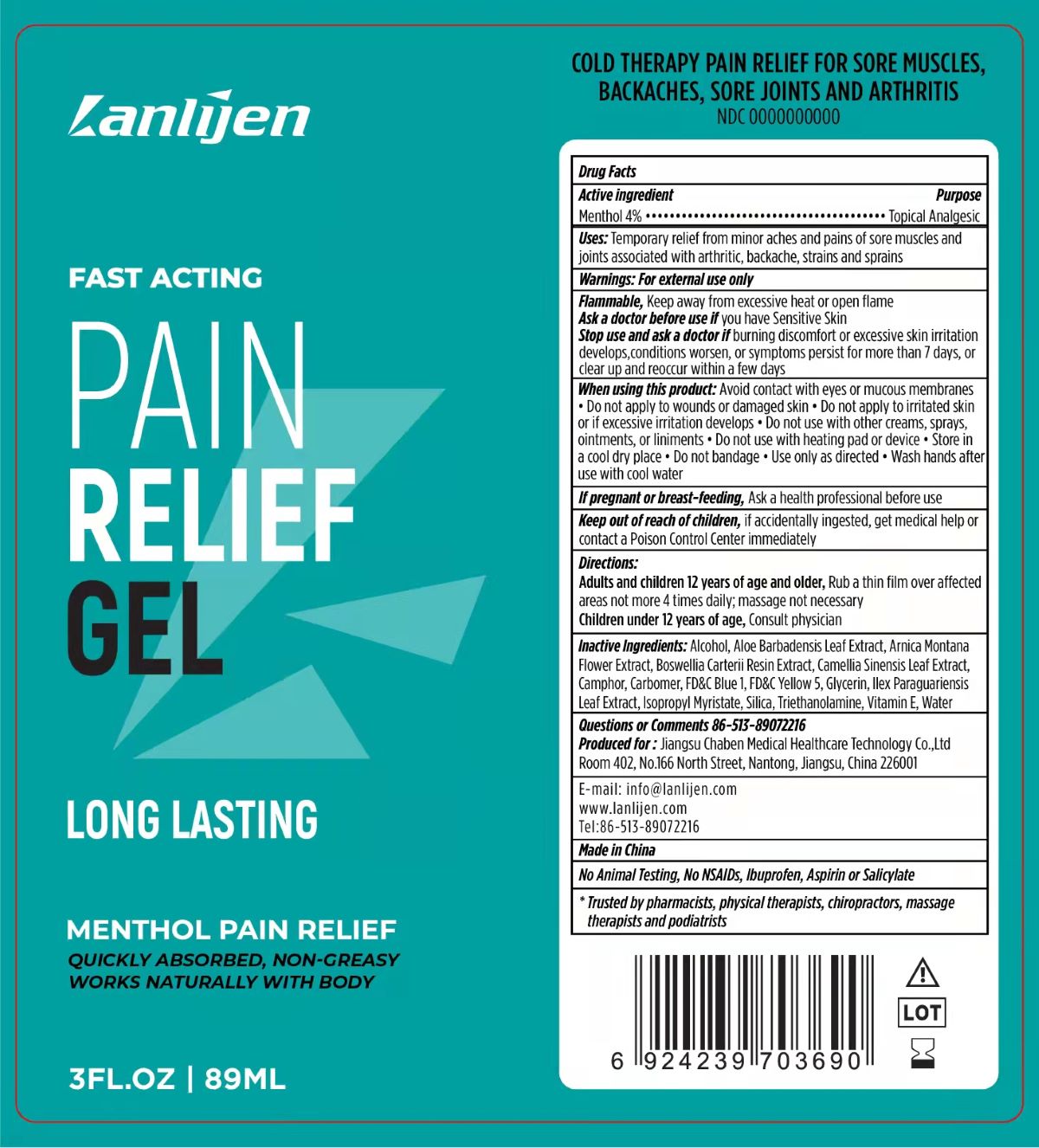 DRUG LABEL: Lanlijen Menthol Pain Relief
NDC: 83050-232 | Form: GEL
Manufacturer: Jiangsu Chaben Medical Healthcare Technology Co.,Ltd
Category: otc | Type: HUMAN OTC DRUG LABEL
Date: 20221213

ACTIVE INGREDIENTS: MENTHOL 0.04 g/1 g
INACTIVE INGREDIENTS: FD&C BLUE NO. 1; POLYACRYLIC ACID (250000 MW); WATER; CAMPHOR (SYNTHETIC); SILICON DIOXIDE; ISOPROPYL MYRISTATE; ILEX PARAGUARIENSIS LEAF; .ALPHA.-TOCOPHEROL, D-; ALOE VERA LEAF; ARNICA MONTANA FLOWER; GLYCERIN; FRANKINCENSE; ALCOHOL; GREEN TEA LEAF; TROLAMINE; FD&C YELLOW NO. 5

Lanlijen, Menthol Pain Relief, 3fl.oz/89ml, Gel

Active ingredient

Menthol 4.0% w/w ...... Purpose: Topical Analgesic

Purpose

Topical Analgesic

Uses

Temporary relief from minor aches and pains of sore muscles and joints associated with arthritic, backache, strains and sprains

Warnings

For external use only

Flammable, Keep away from excessive heat or open flame

Ask a doctor before use if you have Sensitive Skin

Stop use and ask a doctor if burning discomfort or excessive skin irritation develops, conditions worsen, or symptoms persist for more than 7 days, or clear up and reoccur within a few days

Ask a doctor before use if you have Sensitive Skin

Stop use and ask a doctor if burning discomfort or excessive skin irritation develops, conditions worsen, or symptoms persist for more than 7 days, or clear up and reoccur within a few days

Stop use and ask a doctor if burning discomfort or excessive skin irritation develops, conditions worsen, or symptoms persist for more than 7 days, or clear up and reoccur within a few days

When using this product

Avoid contact with eyes or mucous membranes • Do not apply to wounds or damaged skin • Do not apply to irritated skin or if excessive irritation develops • Do not use with other creams, sprays, ointments, or liniments • Do not use with heating pad or device • Store in a cool dry place • Do not bandage • Use only as directed • Wash hands after use with cool water

DO NOT USE

• Do not apply to wounds or damaged skin • Do not apply to irritated skin or if excessive irritation develops • Do not use with other creams, sprays, ointments, or liniments • Do not use with heating pad or device

STORAGE AND HANDLING

• Store in a cool dry place

If pregnant or breast-feeding

Ask a health professional before use

Keep out of reach of children

If accidentally ingested, get medical help or contact a Poison Control Center immediately

Directions

Adults and children 12 years of age and older, Rub a thin film over affected areas not more 4 times daily; massage not necessary

Children under 12 years of age, Consult physician

ASK DOCTOR/PHARMACIST

Children under 12 years of age, Consult physician

Inactive Ingredients

Alcohol, Aloe Barbadensis Leaf Extract, Arnica Montana Flower Extract, Boswellia Carterii Resin Extract, Camellia Sinensis Leaf Extract, Camphor, Carbomer, FD&C Blue 1, FD&C Yellow 5, Glycerin, llex Paraguariensis Leaf Extract, Isopropyl Myristate, Silica, Triethanolamine, Vitamin E, Water

Questions or Comments

86-513-89072216

E-mail: info@lanlijen.com
www.lanlijen.com
Tel:86-513-89072216

OTHER SAFETY INFORMATION

No Animal Testing, No NSAIDs, lbuprofen, Aspirin or Salicylate